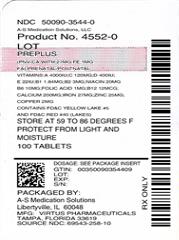 DRUG LABEL: Preplus
NDC: 50090-3544 | Form: TABLET
Manufacturer: A-S Medication Solutions
Category: other | Type: DIETARY SUPPLEMENT
Date: 20210301

ACTIVE INGREDIENTS: VITAMIN A ACETATE 4000 [iU]/1 1; ASCORBIC ACID 120 mg/1 1; CHOLECALCIFEROL 400 [iU]/1 1; .ALPHA.-TOCOPHEROL ACETATE, DL- 22 [iU]/1 1; THIAMINE MONONITRATE 1.84 mg/1 1; RIBOFLAVIN 3 mg/1 1; NIACINAMIDE 20 mg/1 1; PYRIDOXINE HYDROCHLORIDE 10 mg/1 1; FOLIC ACID 1 mg/1 1; CYANOCOBALAMIN 12 ug/1 1; CALCIUM 200 mg/1 1; FERROUS FUMARATE 27 mg/1 1; ZINC OXIDE 25 mg/1 1; CUPRIC OXIDE 2 mg/1 1
INACTIVE INGREDIENTS: MICROCRYSTALLINE CELLULOSE; STEARIC ACID; CROSCARMELLOSE SODIUM; MAGNESIUM STEARATE; SILICON DIOXIDE; FD&C RED NO. 40; ALUMINUM OXIDE; FD&C BLUE NO. 2; FD&C YELLOW NO. 5

PrePLUS tablet

HEALTH CLAIM

Supplement Facts
Serving Size: 1 Tablet
 | Amount Per Serving | %Daily Value for Pregnant and Lactating Women
Vitamin A (as Acetate and Beta Carotene) | 4000 IU | 50%
Vitamin C (Ascorbic Acid) | 120 mg | 200%
Vitamin D (Vitamin D3 as cholecalciferol) | 400 IU | 100%
Vitamin E (dl-Alpha Tocopheryl Acetate) | 22 IU | 73%
Thiamine (Vitamin B1 from Thiamine Mononitrate) | 1.84 mg | 108%
Riboflavin (Vitamin B2) | 3 mg | 150%
Niacin (Niacinamide) | 20 mg | 100%
Vitamin B6 (as Pyridoxine HCl) | 10 mg | 400%
Folic Acid | 1 mg | 125%
Vitamin B12 (Cyanocobalamin) | 12 mcg | 150%
Calcium | 200 mg | 15%
Iron (Ferrous Fumarate) | 27 mg | 150%
Zinc (Zinc Oxide) | 25 mg | 167%
Copper (Cupric Oxide) | 2 mg | 100%

Other Ingredients: Microcrystalline Cellulose Kosher, Stearic Acid Kosher, Croscarmellose Sodium Kosher, Magnesium Stearate Kosher, Silicon Dioxide Kosher, FD&C Red #40 (Lakes), FD&C Blue #2 Aluminum Lake, and FD&C Yellow Lake #5.

Contains FD&C Red #40 (Lakes), FD&C Blue #2 Aluminum Lake, and FD&C Yellow Lake #5.

DESCRIPTION

PrePLUS (PNV-Ca with 27 mg Fe; 1 mg FA) Tablet is an orally administered prenatal/postnatal prescription folic acid-containing dietary supplement and should be administered under the supervision of a licensed medical practitioner.

DOSAGE AND ADMINISTRATION

Before, during and/or after pregnancy, one tablet daily, with a meal, or as directed by a licensed healthcare practitioner regardless of lactation status.

WARNINGS

WARNING: Accidental overdose of iron-containing products is a leading cause of fatal poisoning in children under 6. Keep this product out of reach of children. In case of accidental overdose, call a doctor or poison control center immediately.

CAUTION

High levels of folic acid may, especially in older adults, hide signs of Vitamin B-12 deficiency (such as pernicious anemia), a condition that can cause nerve damage.

SAFE HANDLING WARNING

Store at 15° – 30°C (59° – 86°F). [See USP Controlled Room Temperature.] Protect from light and moisture. Dispense in a tight, light-resistant container. Notice: Contact with moisture may produce surface discoloration or erosion.

HEALTH CLAIM

Call your licensed medical practitioner about side effects. You may report side effects by calling Virtus at 1-888-848-3593 or 1-800-FDA-1088.

HOW SUPPLIED

Supplied as beige tablet, imprinted "V258" dispensed in bottles of 500 tablets.

HEALTH CLAIM

Manufactured for:
Virtus Pharmaceuticals, LLC
Tampa, Florida 33619
1-888-848-3593

Rev. 03/15